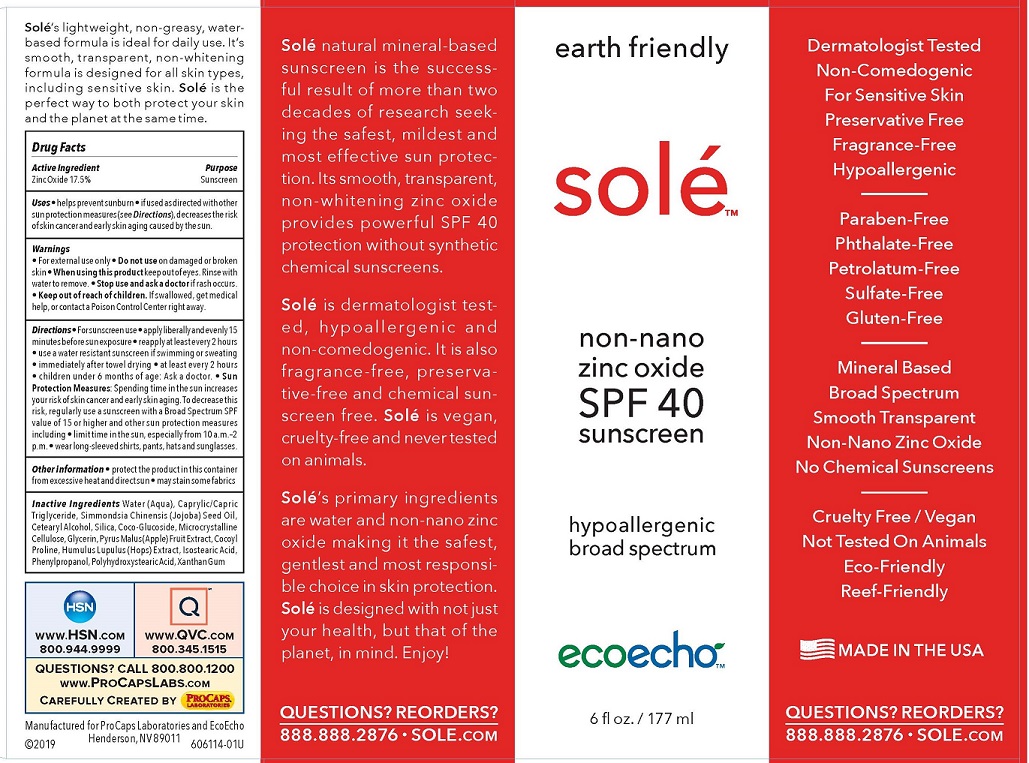 DRUG LABEL: NON-NANO SUNSCREEN
NDC: 72879-505 | Form: LOTION
Manufacturer: ProCaps Laboratories, Inc.
Category: otc | Type: HUMAN OTC DRUG LABEL
Date: 20190227

ACTIVE INGREDIENTS: ZINC OXIDE 17.5 g/100 mL
INACTIVE INGREDIENTS: WATER; MEDIUM-CHAIN TRIGLYCERIDES; JOJOBA OIL; CETOSTEARYL ALCOHOL; SILICON DIOXIDE; COCO-GLYCERIDES; MICROCRYSTALLINE CELLULOSE; GLYCERIN; APPLE; COCOYL PROLINE; HOPS; ISOSTEARIC ACID; PHENYLPROPANOL; POLYHYDROXYSTEARIC ACID (2300 MW); XANTHAN GUM

Solé non-nano zinc oxide SPF 40 sunscreen

ACTIVE INGREDIENT

Zinc Oxide 17.5%

PURPOSE

Sunscreen

USE

- For external use only
- Do not use on damaged or broken skin
- When using this product keep out of eyes. Rinse with water to remove.
- Stop use and ask a doctor if rash occurs.
- Keep out of reach of children. If swallowed, get medical help, or contact a Poison Control Center right away.

DIRECTIONS

- For sunscreen use
- apply liberally and evenly 15minutes before sun exposure
- reapply at least every 2 hours
- use a water resistant sunscreen if swimming or sweating
- immediately after towel drying
- at least every 2 hours
- children under 6 months of age: Ask a doctor.
- Sun Protection Measures: Spending time in the sun increasesyour risk of skin cancer and early skin aging. To decrease this risk, regularly use a sunscreen with a Broad Spectrum SPF value of 15 or higher and other sun protection measuresincluding
- limit time in the sun, especially from 10 a.m.–2 p.m.
- wear long-sleeved shirts, pants, hats and sunglasses.

OTHER INFORMATION

- protect the product in this container from excessive heat and direct sun
- may stain some fabrics

QUESTIONS?

CALL 800.800.1200
www.ProCapsLabs.com

INACTIVE INGREDIENTS

Water (Aqua), Caprylic/Capric Triglyceride, Simmondsia Chinensis (Jojoba) Seed Oil, Cetearyl Alcohol, Silica, Coco-Glucoside, Microcrystalline Cellulose, Glycerin, Pyrus Malus (Apple) Fruit Extract, Cocoyl Proline, Humulus Lupulus (Hops) Extract, Isostearic Acid, Phenylpropanol, Polyhydroxystearic Acid, Xanthan Gum